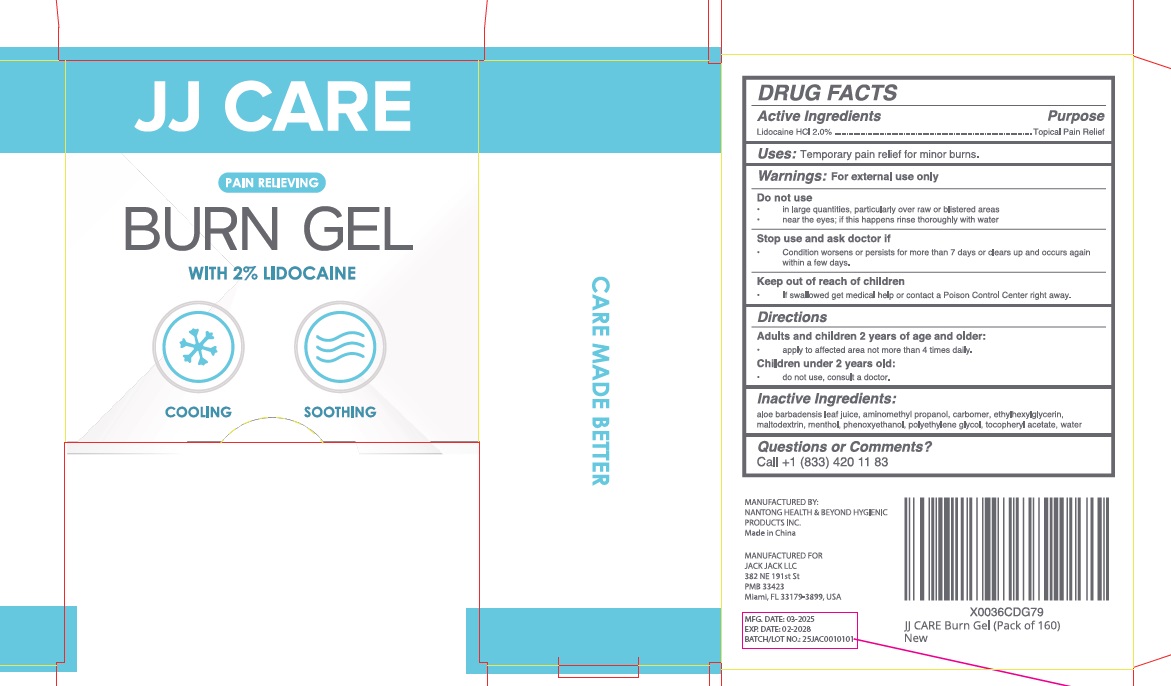 DRUG LABEL: JJ Care BURN
NDC: 43473-069 | Form: GEL
Manufacturer: Nantong Health & Beyond Hygienic Products Inc.
Category: otc | Type: HUMAN OTC DRUG LABEL
Date: 20250219

ACTIVE INGREDIENTS: LIDOCAINE HYDROCHLORIDE 2 g/100 g
INACTIVE INGREDIENTS: WATER; ALOE VERA LEAF; CARBOMER 934; MENTHOL; ETHYLHEXYLGLYCERIN; MALTODEXTRIN; PHENOXYETHANOL; PROPYLENE GLYCOL; AMINOMETHYL PROPANOL; .ALPHA.-TOCOPHEROL ACETATE

43473-069 JJ Care Burn Gel

Active ingredient

Lidocaine HCI 2%

Purpose

Topical Pain Relief

Uses

Temporary pain relief for minor burns.

Warnings

For external use only.

Do not use

■ in large quantities, particularly over raw or blistered areas

■ near eyes, if this happens rinse thoroughly with water

Stop use and ask a doctorif the condition worsens or persists for more than 7 days or clears up and occurs again

Keep out of reach of children. If swallowed, get medical help or contact a Poison Control Center right away

Directions

Adults and children 2 years of age or older

■ Apply to affected area not more than 4 times daily

Chilrdren under 2 years old

■ Do not use, consult a doctor

Inactive ingredients

Aloe Barbadensis Leaf Juice, Aminomethyl Propanol, Carbomer, Ethylhexgilglycerin, Maltodextrin, Menthol, Phenoxyethanol, Polyethylene Glycol, Tocopheryl Acetate, Water.